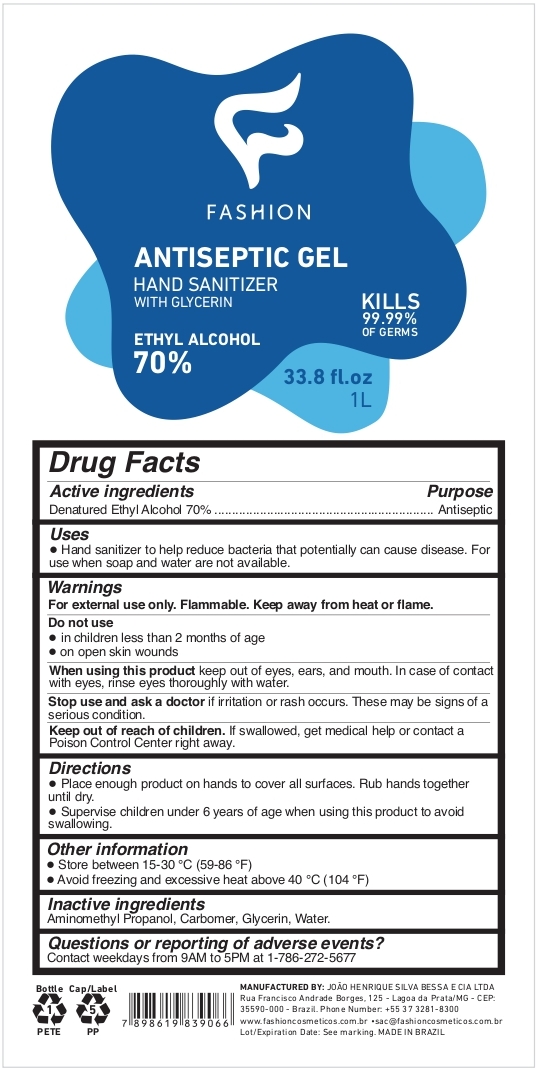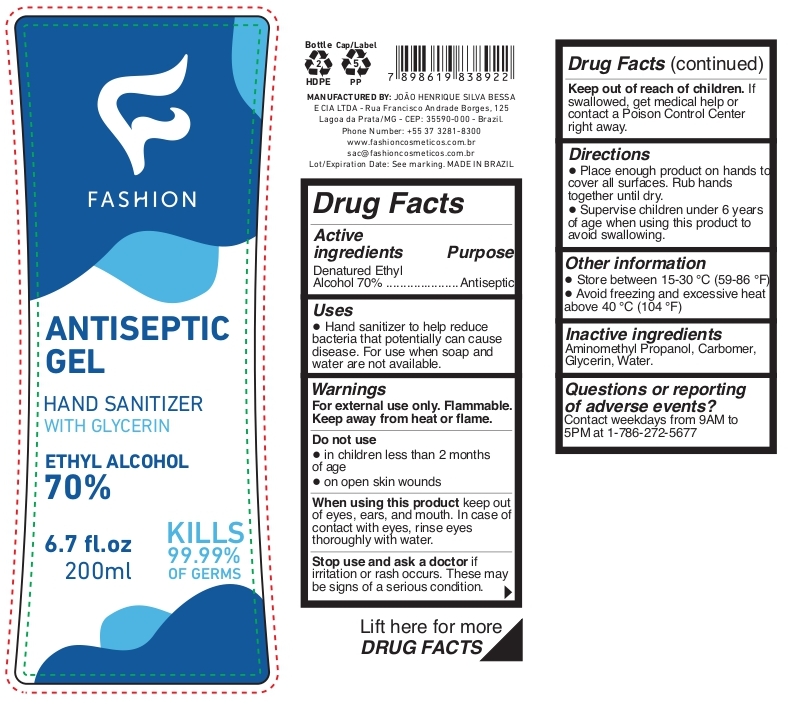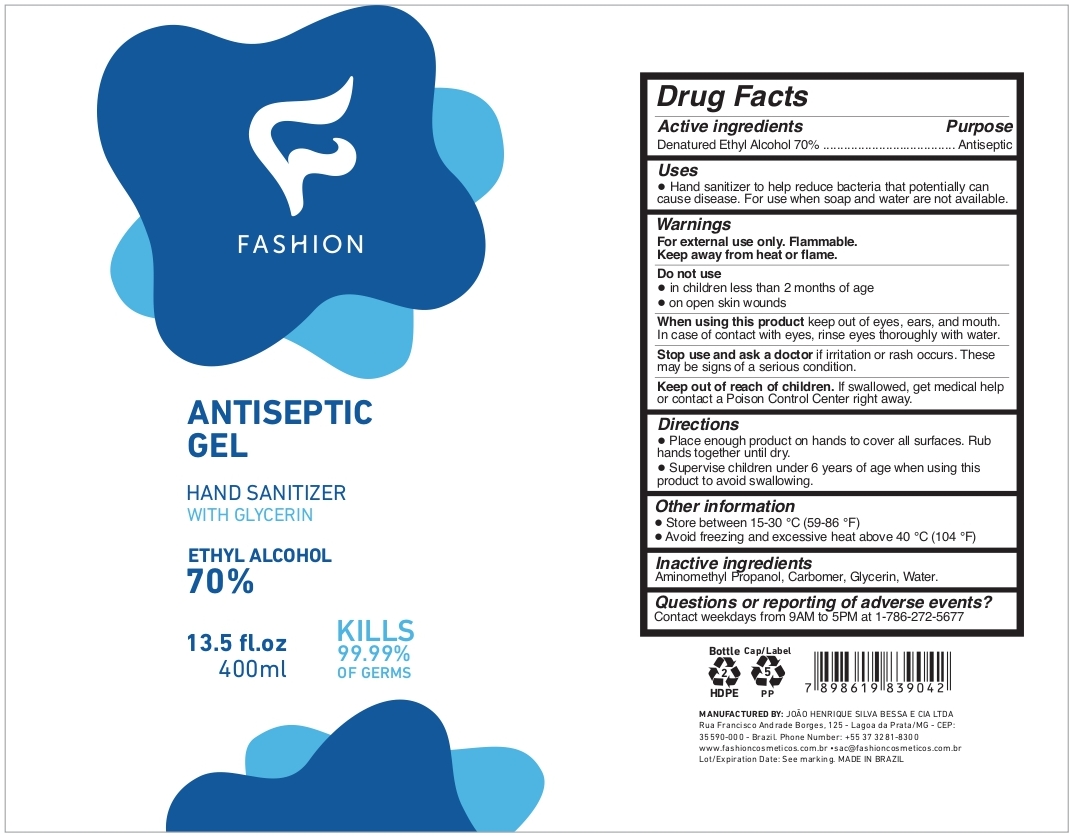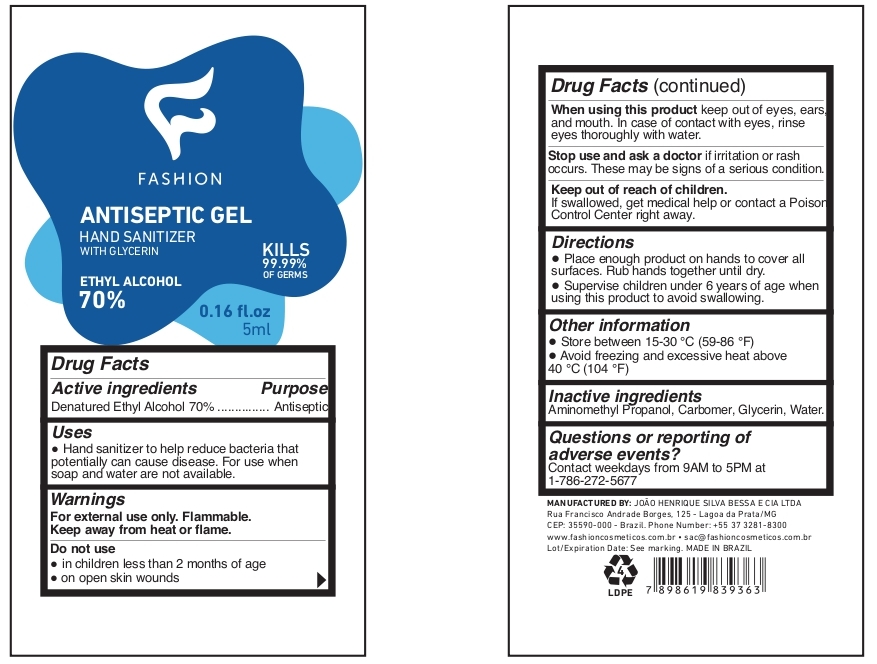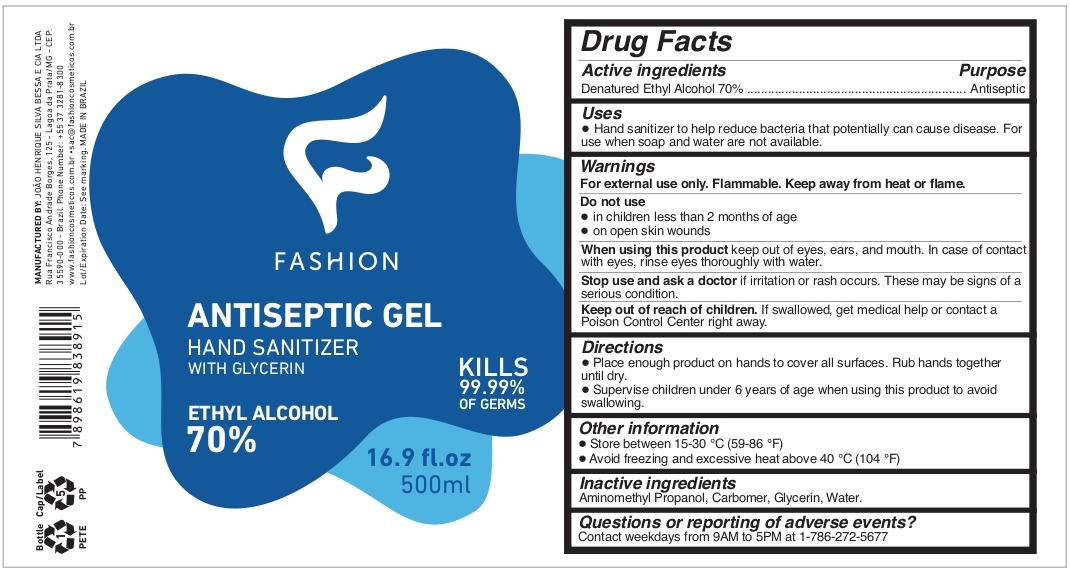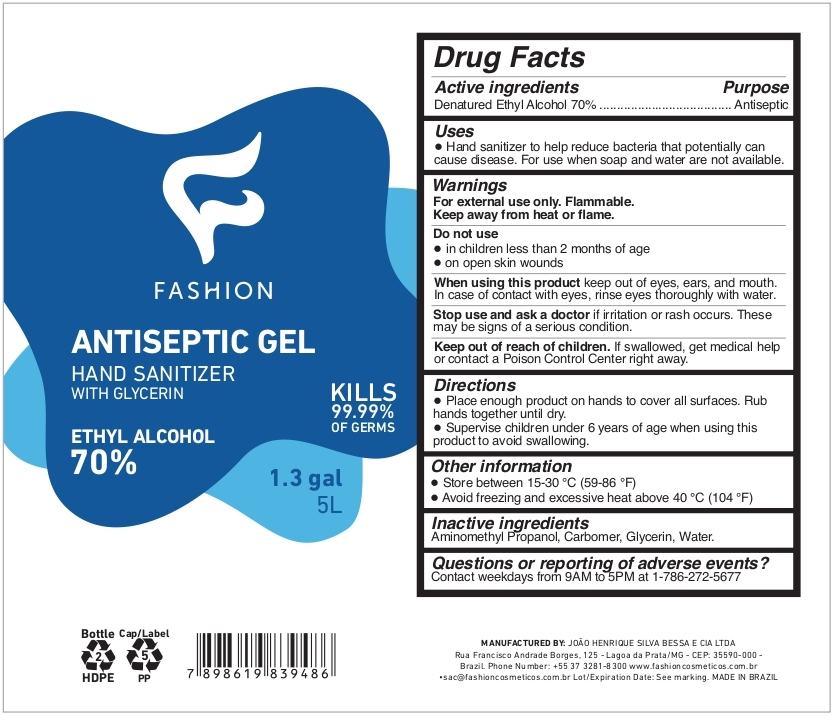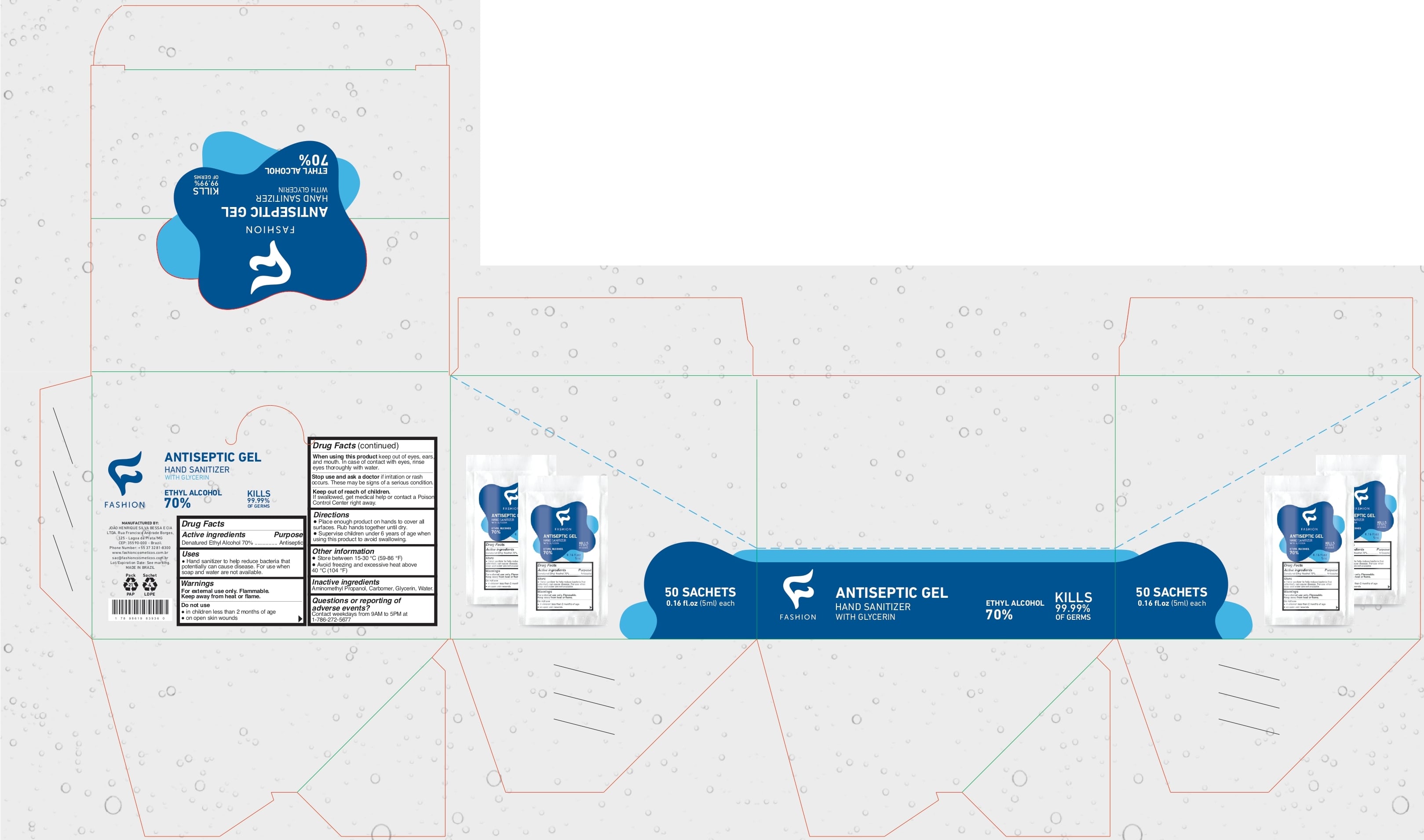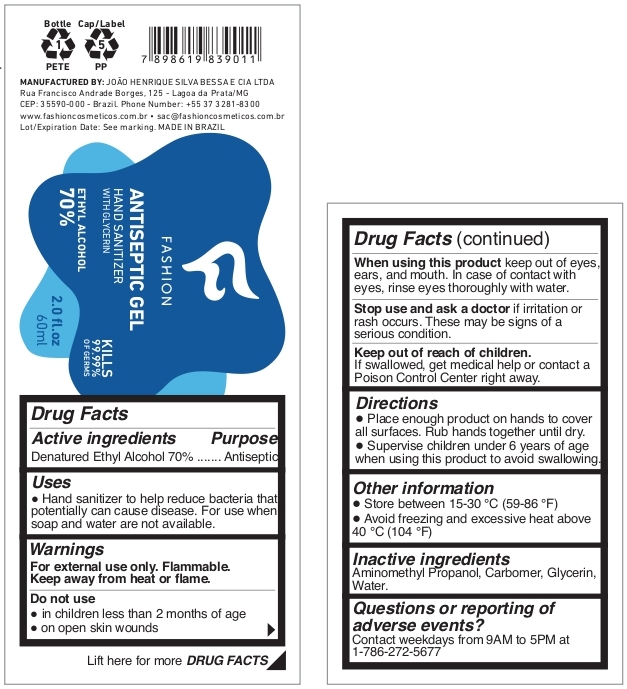 DRUG LABEL: Fashion Antiseptic Gel Hand Sanitizer
NDC: 78904-001 | Form: GEL
Manufacturer: JOAO HENRIQUE SILVA BESSA E CIA LTDA
Category: otc | Type: HUMAN OTC DRUG LABEL
Date: 20201228

ACTIVE INGREDIENTS: ALCOHOL 70 mL/100 mL
INACTIVE INGREDIENTS: WATER 26.35 mL/100 mL; GLYCERIN 3 mL/100 mL; AMINOMETHYLPROPANOL 0.3 mL/100 mL; CARBOMER 940 0.35 mL/100 mL

NO CHANGE NOTIFICATION

Drug Facts Panel - Active Ingredients

Denatured Ethyl Alcohol 70%. Purpose: Antiseptic

Drug Facts Panel - Purpose

Purpose: Antiseptic.

Drug Facts Panel - Uses

Use: Hand sanitizer to help reduce bacteria that potentially can cause disease. For use when soap and water are not available.

Drug Facts Panel - Warnings

For external use only. Flammable. Keep away from heat or flame.
Do not use
● in children less than 2 months of age
● on open skin wounds
When using this product keep out of eyes, ears, and mouth. In case of contact with eyes, rinse eyes thoroughly with water.
Stop use and ask a doctor if irritation or rash occurs. These may be signs of a serious condition.
Keep out of reach of children. If swallowed, get medical help or contact a Poison Control Center right away.

Do not use
● in children less than 2 months of age
● on open skin wounds

When using this product keep out of eyes, ears, and mouth. In case of contact with eyes, rinse eyes thoroughly with water.

Stop use and ask a doctor if irritation or rash occurs. These may be signs of a serious condition.

Stop use and ask a doctor if irritation or rash occurs. These may be signs of a serious condition.

Keep out of reach of children. If swallowed, get medical help or contact a Poison Control Center right away.

Drug Facts Panel - Directions

Directions:

● Place enough product on hands to cover all surfaces. Rub hands together until dry.
● Supervise children under 6 years of age when using this product to avoid swallowing.

Drug Facts Panel - Other Information

Other information:
● Store between 15-30 °C (59-86 °F)
● Avoid freezing and excessive heat above 40 °C (104 °F)

Drug Facts Panel - Inactive Ingredients

Inactive ingredients:
Aminomethyl Propanol, Carbomer, Glycerin, Water.

Drug Facts Panel - Question and reporting of adverse events

Questions or reporting of adverse events?
Contact weekdays from 9AM to 5PM at 1-786-272-5677

Package Label - Principal Display Panel

60 ml NDC 78904-001-01

200 ml NDC 78904-001-02

400 ml NDC 78904-001-03

500 ml NDC 78904-001-04

1000 ml NDC 78904-001-05

5000 ml NDC 78904-001-06

5 ml NDC 78904-001-07

Level 1

50x5 ml NDC 78904-001-07

Level 2